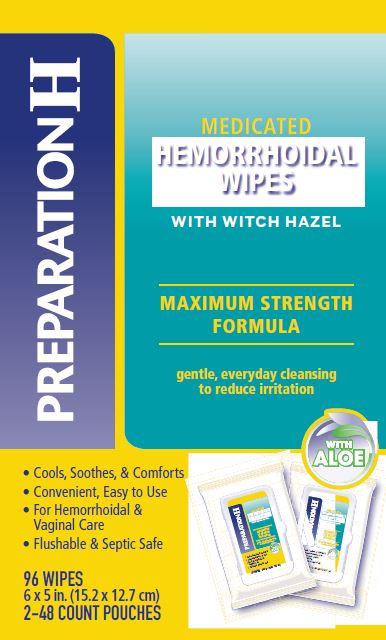 DRUG LABEL: PREPARATION H MEDICATED WIPES
NDC: 0573-0556 | Form: CLOTH
Manufacturer: Haleon US Holdings LLC
Category: otc | Type: HUMAN OTC DRUG LABEL
Date: 20240821

ACTIVE INGREDIENTS: WITCH HAZEL 5 g/1 1
INACTIVE INGREDIENTS: ALOE VERA LEAF; ANHYDROUS CITRIC ACID; CAPRYL/CAPRAMIDOPROPYL BETAINE; DIAZOLIDINYL UREA; GLYCERIN; METHYLPARABEN; PROPYLENE GLYCOL; PROPYLPARABEN; SODIUM CITRATE, UNSPECIFIED FORM; WATER

Drug Facts

Active ingredient

Witch hazel 50%

Purpose

Astringent

Uses

- helps relieve the local itching and discomfort associated with hemorrhoids
- temporary relief of irritation and burning
- aids in protecting irritated anorectal areas

Warnings

For external use only

When using this product

- do not exceed the recommended daily dosage unless directed by a doctor
- do not put this product into the rectum by using fingers or any mechanical device or applicator

Stop use and ask a doctor if

- bleeding occurs
- condition worsens or does not improve within 7 days

Keep out of reach of children.

If swallowed, get medical help or contact a Poison Control Center right away.

Directions

- open the lid on the top of the wipes pouch
- peel back wipes seal, remove completely and discard
- grab the top wipe at the edge of the center fold and pull out of pouch
- close lid after each use to retain moisture
- adults: unfold wipe and cleanse the area by gently wiping, patting or blotting. If necessary, repeat until all matter is removed from the area
- use up to 6 times daily or after each bowel movement and before applying topical hemorrhoidal treatments, and then discard
- children under 12 years of age: consult a doctor

Other information

- for best results, flush only one or two wipes at a time
- store at 20-25°C (68-77°F)

Inactive ingredients

aloe barbadensis leaf juice, anhydrous citric acid, capryl/capramidopropyl betaine, diazolidinyl urea, glycerin, methylparaben, propylene glycol, propylparaben, purified water, sodium citrate

Questions or comments?

Call weekdays 9 AM to 5 PM EST at 1-800-99PrepH or 1-800-997-7374

Other Uses

- for vaginal care cleanse the area by gently wiping, patting or blotting. Repeat as needed.
- for use as a moist compress – if necessary, first cleanse the area as previously described. Fold new wipe to desired size and place in contact with tissue for a soothing and cooling effect. Leave in place for up to 15 minutes and repeat as needed.

Generic Section

Preparation H® Medicated Wipes are made with advanced wipe technology, have been scientifically tested to be flushable and are safe for well-maintained sewer and septic systems*. They are made with 100% plant-based materials and are free from chemical binders.

*Not recommended for use with basement pump systems. Flush only one wipe at a time.

Principle Display Panel

PREPARATION H

MEDICATED
HEMMORHOIDAL
WIPES
WITH WITCH HAZEL

MAXIMUM STRENGTH FORMULA

gentle, everyday cleansing to reduce irritation

WITH ALOE

- Cools, Soothes, & Comforts
- Convenient, Easy to Use
- For Hemorrhoidal & Vaginal Care
- Flushable & Septic Safe

96 WIPES

6 X 5 in. (15.2 x 12.7 cm)

2-48 COUNT POUCHES